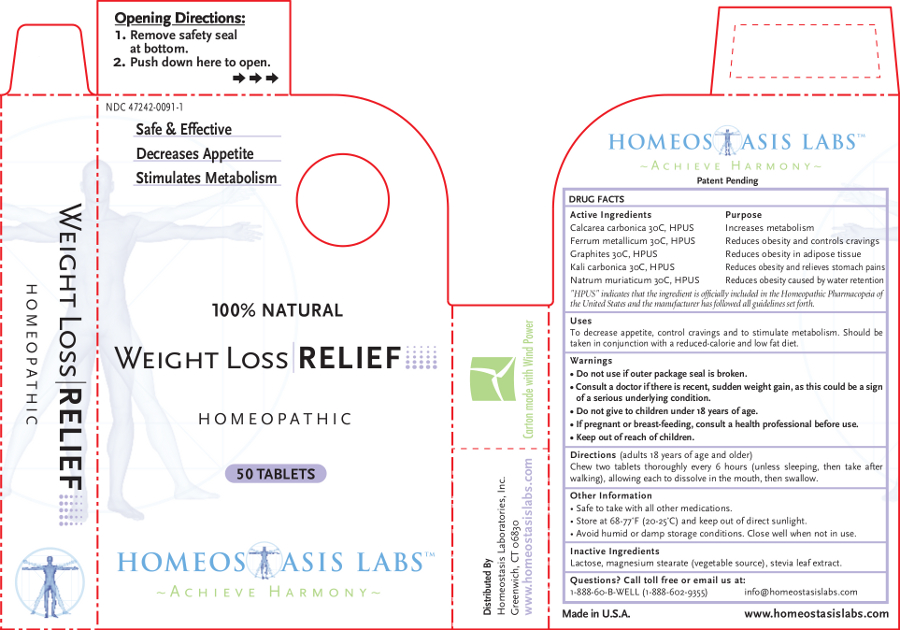 DRUG LABEL: Weight Loss RELIEF
NDC: 47242-0091 | Form: TABLET, CHEWABLE
Manufacturer: Homeostasis Laboratories, Inc.
Category: homeopathic | Type: HUMAN OTC DRUG LABEL
Date: 20121114

ACTIVE INGREDIENTS: OYSTER SHELL CALCIUM CARBONATE, CRUDE 30 [hp_C]/1 1; IRON 30 [hp_C]/1 1; GRAPHITE 30 [hp_C]/1 1; POTASSIUM CARBONATE 30 [hp_C]/1 1; SODIUM CHLORIDE 30 [hp_C]/1 1
INACTIVE INGREDIENTS: LACTOSE; MAGNESIUM STEARATE; STEVIA REBAUDIUNA LEAF

Weight Loss RELIEF

Active Ingredients | Purpose
Calcarea carbonica 30C, HPUS | Increases metabolism
Ferrum metallicum 30C, HPUS | Reduces obesity and controls cravings
Graphites 30C, HPUS | Reduces obesity in adipose tissue
Kali carbonica 30C, HPUS | Reduces obesity and relieves stomach pains
Natrum muriaticum 30C, HPUS | Reduces obesity caused by water retention

"HPUS" indicates that the ingredient is officially included in the Homeopathic Pharmacopeia of the United States and the manufacturer has followed all guidelines set forth.

Uses

To decrease appetite, control cravings and to stimulate metabolism.

Should be taken in conjunction with a reduced-calorie and low fat diet.

Warnings

- Do not use if outer package seal is broken.
- Consult a doctor if there is recent, sudden weight gain, as this could be a sign of a serious underlying condition.
- Do not give to children under 18 years of age.

PREGNANCY OR BREAST FEEDING

- If pregnant or breast-feeding, consult a health professional before use.

- Keep out of reach of children.

Directions

(adults 18 years of age and older)

Chew two tablets thoroughly every 6 hours (unless sleeping, then take after walking), allowing each to dissolve in the mouth, then swallow.

Other information

- Safe to take with all other medications.
- Store at 68-77°F (20-25°C) and keep out of direct sunlight.
- Avoid humid or damp storage conditions. Close well when not in use.

Inactive Ingredients

Lactose, magnesium stearate (vegetable source), stevia leaf extract.

Questions? Call toll free or email us at:

1-888-60-B-WELL (1-888-602-9355)

info@homeostasislabs.com